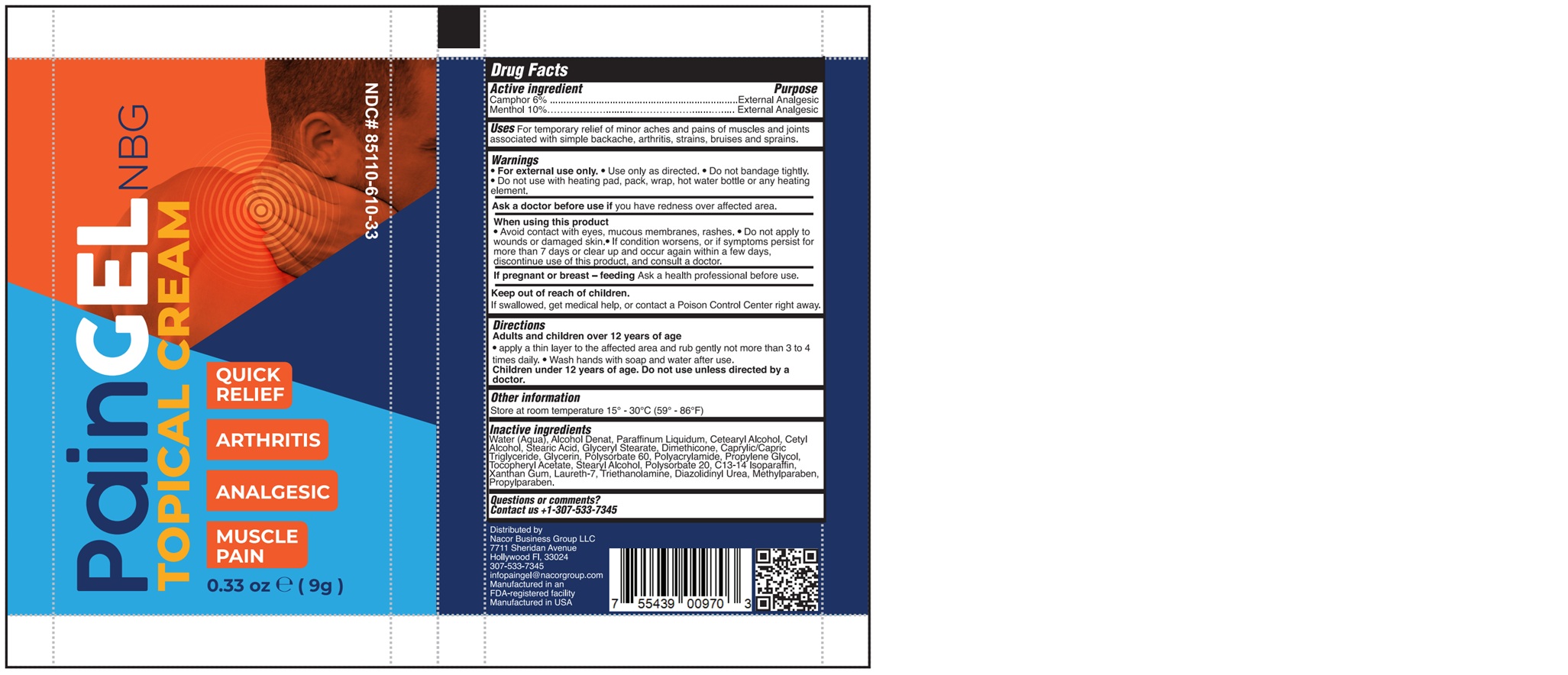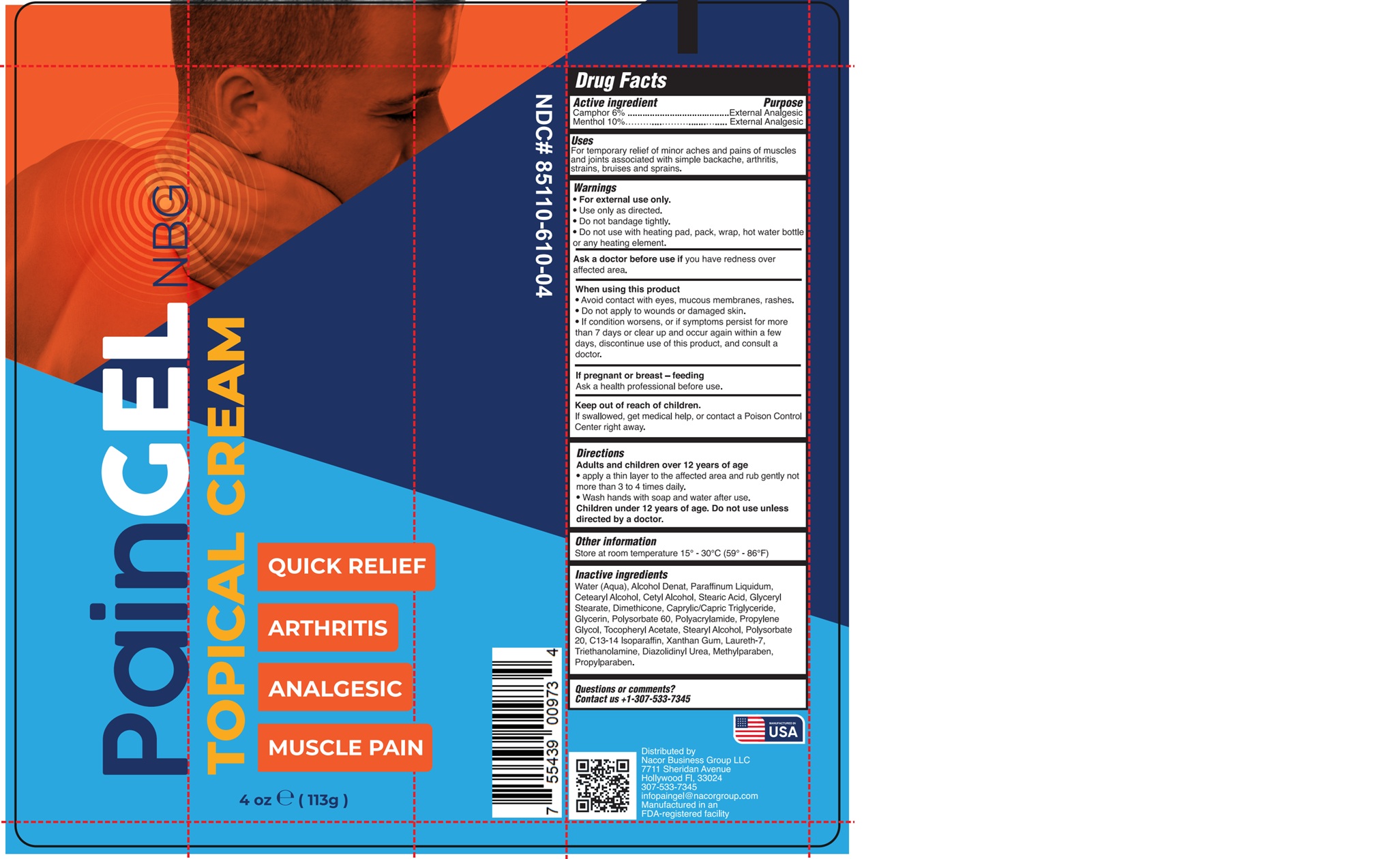 DRUG LABEL: PAINGEL
NDC: 85110-610 | Form: CREAM
Manufacturer: NACOR BUSINESS GROUP LLC
Category: otc | Type: HUMAN OTC DRUG LABEL
Date: 20251106

ACTIVE INGREDIENTS: MENTHOL 10 g/100 g; CAMPHOR (SYNTHETIC) 6 g/100 g
INACTIVE INGREDIENTS: DIAZOLIDINYL UREA; C13-14 ISOPARAFFIN; XANTHAN GUM; STEARYL ALCOHOL; POLYSORBATE 20; METHYLPARABEN; PROPYLPARABEN; LAURETH-7; TRIETHANOLAMINE; CETEARYL ALCOHOL; WATER; GLYCERIN; CETYL ALCOHOL; STEARIC ACID; GLYCERYL STEARATE; DIMETHICONE; CAPRYLIC/CAPRIC TRIGLYCERIDE; POLYACRYLAMIDE (1500 MW); ROSMARINUS OFFICINALIS WHOLE; PROPYLENE GLYCOL; PARAFFINUM LIQUIDUM; ALCOHOL; POLYSORBATE 60; .ALPHA.-TOCOPHEROL ACETATE

85110-610-04
85110-610-33

Active ingredients

Camphor ………………. 6%

Menthol …………….…. 10%

Purpose

External Analgesic

Use

For temporary relief of minor aches and pains of muscles and joints associated with simple backache, arthritis, strains, bruises and sprains.

WARNINGS

- For external use only.
- Use only as directed.
- Do not bandage tightly.
- Do not use with heating pad, pack, wrap, hot water bottle or any heating element.

Ask a doctor before use if

you have redness over affected area.

When using this product

- Avoid contact with eyes, mucous membranes, rashes.
- Do not apply to wounds or damaged skin.
- If condition worsens, or if symptoms persist for more than 7 days or clear up and occur again within a few days, discontinue use of this product, and consult a doctor.

If pregnant of breast feeding

Ask a health professional before use.

KEEP OUT OF REACH OF CHILDREN

If swallowed, get medical help or contact a Poison Control Center right away.

Directions

Adults and children over 12 years of age

- apply a thin layer to the affected area and rub gently not more than 3 to 4 times daily.
- Wash hands with soap and water after use.

Children under 12 years of age. Do not use unless directed by a doctor.

Other information

Store at room temperature 15° - 30°C (59° - 86°F)

INACTIVE INGREDIENT

Water (Aqua), Alcohol Denat, Paraffinum Liquidum, Cetearyl Alcohol, Cetyl Alcohol, Stearic Acid, Glyceryl Stearate, Dimethicone, Caprylic/Capric Triglyceride, Glycerin, Polysorbate 60, Polyacrylamide, Propylene Glycol, Tocopheryl Acetate, Stearyl Alcohol, Polysorbate 20, C13-14 Isoparaffin, Xanthan Gum, Laureth-7, Triethanolamine, Diazolidinyl Urea, Methylparaben, Propylparaben.

QUESTION OR COMMENTS?

Contact us +1-307-533-7345